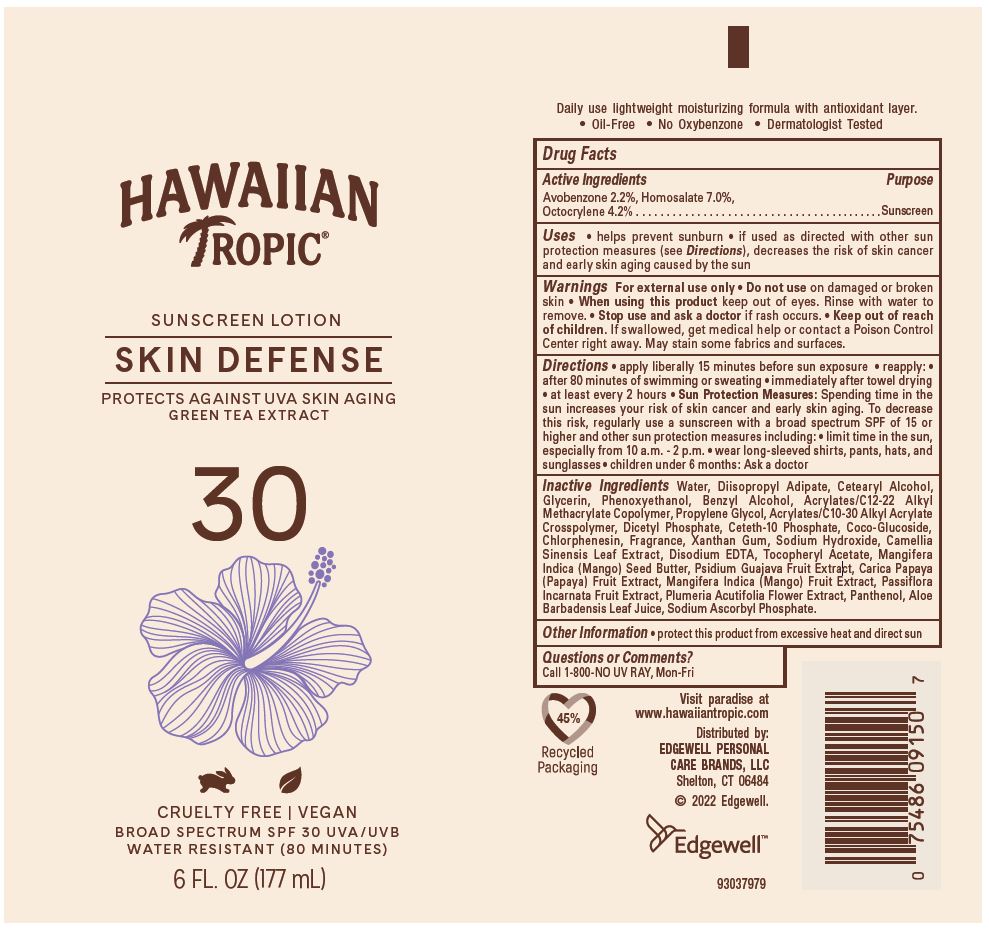 DRUG LABEL: HAWAIIAN TROPIC
NDC: 63354-621 | Form: LOTION
Manufacturer: Edgewell Personal Care Brands LLC
Category: otc | Type: HUMAN OTC DRUG LABEL
Date: 20241027

ACTIVE INGREDIENTS: HOMOSALATE 7 g/100 g; OCTOCRYLENE 4.2 g/100 g; AVOBENZONE 2.2 g/100 g
INACTIVE INGREDIENTS: WATER; DIISOPROPYL ADIPATE; PROPYLENE GLYCOL; CHLORPHENESIN; MANGO; XANTHAN GUM; EDETATE DISODIUM; PANTHENOL; PHENOXYETHANOL; CETOSTEARYL ALCOHOL; BENZYL ALCOHOL; CETETH-10 PHOSPHATE; DIHEXADECYL PHOSPHATE; GREEN TEA LEAF; ALPHA-TOCOPHEROL ACETATE; PLUMERIA RUBRA FLOWER; GLYCERIN; COCO GLUCOSIDE; MANGIFERA INDICA SEED BUTTER; PASSIFLORA INCARNATA FRUIT; GUAVA; SODIUM HYDROXIDE; ALOE VERA LEAF; SODIUM ASCORBYL PHOSPHATE; PAPAYA

Active Ingredients

Avobenzone 2.2%, Homosalate 7.0%, Octocrylene 4.2%

Purpose

Sunscreen

Uses

• helps prevent sunburn • if used as directed with other sun protection measures (see Directions), decreases the risk of skin cancer and early skin aging caused by the sun

Warnings

For external use only

May stain some fabrics and surfaces.

Do not use

on damaged or broken skin

When using this product

keep out of eyes. Rinse with water to remove.

Stop use and ask a doctor

if rash occurs.

Keep out of reach of children.

If swallowed, get medical help or contact a Poison Control Center right away.

Directions

• apply liberally 15 minutes before sun exposure • reapply: • after 80 minutes of swimming or sweating • immediately after towel drying • at least every 2 hours • Sun Protection Measures: Spending time in the sun increases your risk of skin cancer and early skin aging. To decrease this risk, regularly use a sunscreen with a broad spectrum SPF of 15 or higher and other sun protection measures including: • limit time in the sun, especially from 10 a.m. - 2 p.m. • wear long-sleeved shirts, pants, hats, and sunglasses • children under 6 months: Ask a doctor

Inactive Ingredients

Water, Diisopropyl Adipate, Cetearyl Alcohol, Glycerin, Phenoxyethanol, Benzyl Alcohol, Acrylates/C12-22 Alkyl Methacrylate Copolymer, Propylene Glycol, Acrylates/C10-30 Alkyl Acrylate Crosspolymer, Dicetyl Phosphate, Ceteth-10 Phosphate, Coco-Glucoside, Chlorphenesin, Fragrance, Xanthan Gum, Sodium Hydroxide, Camellia Sinensis Leaf Extract, Disodium EDTA, Tocopheryl Acetate, Mangifera Indica (Mango) Seed Butter, Psidium Guajava Fruit Extract, Carica Papaya (Papaya) Fruit Extract, Mangifera Indica (Mango) Fruit Extract, Passiflora Incarnata Fruit Extract, Plumeria Acutifolia Flower Extract, Panthenol, Aloe Barbadensis Leaf Juice, Sodium Ascorbyl Phosphate.

Other Information

• protect this product from excessive heat and direct sun

Questions or Comments?

Call 1-800-NO UV RAY, Mon-Fri

Principal Display Panel

HAWAIIAN
TROPIC®
SUNSCREEN LOTION
SKIN DEFENSE
PROTECTS AGAINST UVA SKIN AGING
GREEN TEA EXTRACT
30
CRUELTY FREE | VEGAN
BROAD SPECTRUM SPF 30 UVA/UVB
WATER RESISTANT (80 MINUTES)
6 FL. OZ (177 mL)